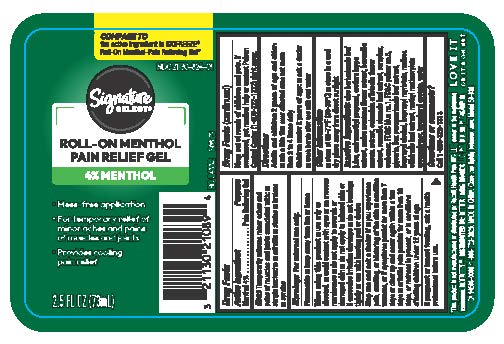 DRUG LABEL: Signature Care Menthol
NDC: 21130-824 | Form: GEL
Manufacturer: Safeway
Category: otc | Type: HUMAN OTC DRUG LABEL
Date: 20241205

ACTIVE INGREDIENTS: MENTHOL 4 g/1 mL
INACTIVE INGREDIENTS: CARBOMER 940; GLYCERIN; .ALPHA.-TOCOPHEROL ACETATE; ALOE VERA LEAF; FD&C BLUE NO. 1; CAMELLIA SINENSIS LEAF; METHYL METHACRYLATE/GLYCOL DIMETHACRYLATE CROSSPOLYMER; WATER; CAMPHOR (NATURAL); ARNICA MONTANA FLOWER; MELISSA OFFICINALIS LEAF; BOSWELLIA SERRATA EXTRACT; ARCTIUM LAPPA WHOLE; CALENDULA OFFICINALIS FLOWER; ISOPROPYL MYRISTATE; AMINOMETHYL PROPANOL; ISOPROPYL ALCOHOL; ILEX PARAGUARIENSIS LEAF; FD&C YELLOW NO. 5

Signature Care Menthol 4% Rollon 2.5 oz

Active Ingredient

Menthol 4%

Purpose

Pain Relieving Gel

Uses

Temporarily relieves minor aches and pains of muscles and joints associated with:

- simple backache
- arthritis
- strains
- bruises
- sprains

Warnings

For External use only

keep away from fire or flame

When using this product

use only as directed

- avoid contact with eyes or mucous membranes
- do not apply to wounds or damaged skin
- do not apply to irritated skin or if excessive irritation develops
- do not bandage tightly or use with heating pad or devise

Stop use and ask a doctor if

- you experience pain, swelling, or blistering of the skin
- condition worsens, or if symptoms persist for more than 7 days or clear up and occur again within a few days
- arthritic pain persists for more than 10 days, or redness is present, or in conditions affecting children under 12 years of age.

If pregnant or breast feeding

ask a health professional before use

Keep out of reach of children and pets

If swallowed, get medical help or contact Poison Control Center (1-800-222-1222) right away

Directions

Adults and children 2 years of age and older

- rub a thin film over affected area not more than 3 to 4 times daily

Children under 2 years of age:

- ask a doctor
- wash hands after use with cool water

Other information

- store at 68-77 F (20-25 C)
- store in a cool dry place away from direct sunlight

Inactive ingredients

Aloe Barbadensis Leaf Juice, Aminomethyl Propanol, Arctium Lappa Extract, Arnica Montana Flower Extract, Boswellia Serrata Extract, Calendula Officinalis Flower Extract, Camellia Sinensis Leaf Extract, Camphor, Carbomer, FD&C BLUE NO.1, FD&C YELLOW NO.5, Glycerin, Ilex Paraguariensis Leaf Extract, Isopropyl Alcohol, Isopropyl myristate, Melissa Officinalis Leaf Extract,

Methyl Methacrylate Crosspolymer,Tocopheryl Acetate, Water

Questions and comments

Call 1-866-326-1313